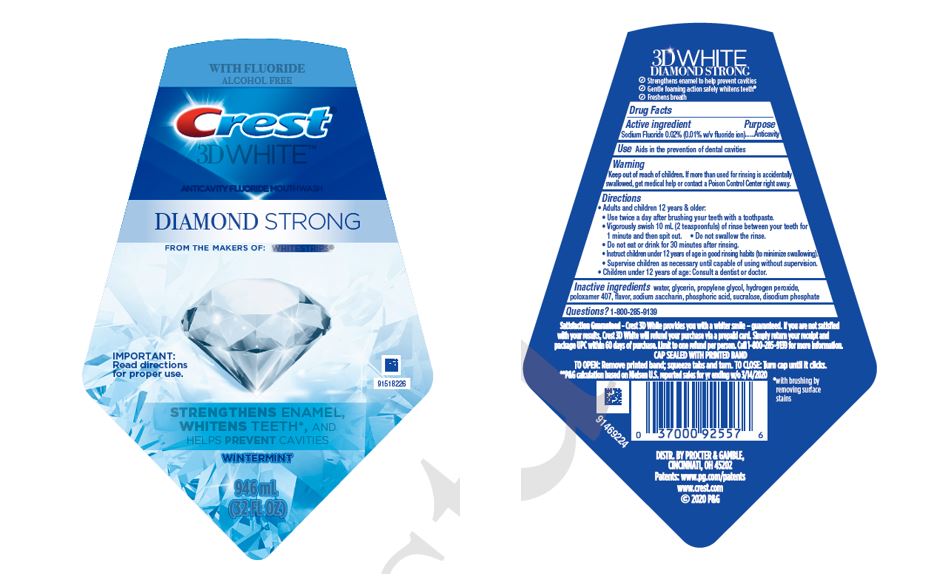 DRUG LABEL: Crest 3D White Luxe
NDC: 37000-862 | Form: RINSE
Manufacturer: The Procter & Gamble Manufacturing Company
Category: otc | Type: HUMAN OTC DRUG LABEL
Date: 20260121

ACTIVE INGREDIENTS: SODIUM FLUORIDE 0.1 mg/1 mL
INACTIVE INGREDIENTS: WATER; GLYCERIN; SUCRALOSE; PROPYLENE GLYCOL; HYDROGEN PEROXIDE; POLOXAMER 407; SACCHARIN SODIUM; PHOSPHORIC ACID; SODIUM PHOSPHATE, DIBASIC, ANHYDROUS

Crest® 3D White Luxe™
Diamond Strong

Drug Facts

Active ingredient

Sodium Fluoride 0.0219% (0.01% w/v fluoride ion)

Purpose

Anticavity

Use

Aids in the prevention of dental cavities

Warning

Keep out of reach of children. If more than used for rinsing is accidentally swallowed, get medical help or contact a Poison Control Center right away.

Directions

- Adults and children 12 years & older:
  - Use twice a day after brushing your teeth with a toothpaste.
  - Vigorously swish 10 mL (2 teaspoonfuls) of rinse between your teeth for 1 minute and then spit out.
  - Do not swallow the rinse.
  - Do not eat or drink for 30 minutes after rinsing.
  - Instruct children under 12 years of age in good rinsing habits (to minimize swallowing).
  - Supervise children as necessary until capable of using without supervision.
- Children under 12 years of age: Consult a dentist or doctor.

Inactive ingredients

water, glycerin, propylene glycol, hydrogen peroxide, poloxamer 407, flavor, sodium saccharin, phosphoric acid, sucralose, disodium phosphate

Questions?

1-800-285-9139

DISTR. BY PROCTER & GAMBLE,
CINCINNATI, OH 45202

PRINCIPAL DISPLAY PANEL - 473 mL Bottle Label

WITH FLUORIDE
ALCOHOL FREE
Crest ®
3D WHITE

ANTICAVITY FLUORIDE MOUTHWASH

DIAMOND STRONG

FROM THE MAKERS OF WHITESTRIPS®

- STRENGTHENS ENAMEL
- WHITENS TEETH
- HELPS PREVENT CAVITIES
- 91518226

WINTERMINT

IMPORTANT: Read directions for proper use.

946 mL
(32 FL OZ)